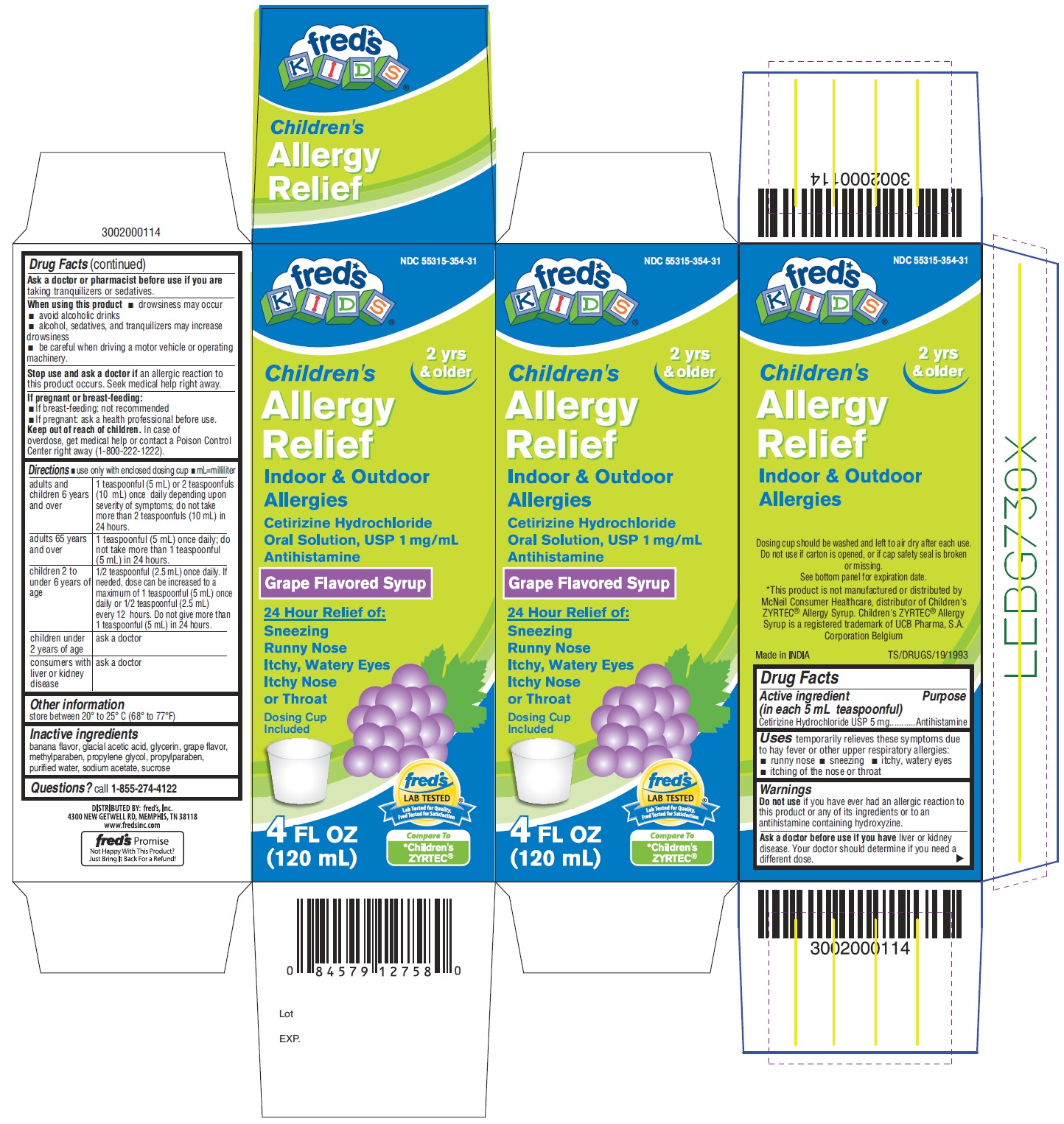 DRUG LABEL: CHILDRENS ALLERGY RELIEF
NDC: 55315-354 | Form: SOLUTION
Manufacturer: Fred's, Inc.
Category: otc | Type: Human OTC Drug Label
Date: 20201213

ACTIVE INGREDIENTS: CETIRIZINE HYDROCHLORIDE 1 mg/1 mL
INACTIVE INGREDIENTS: ACETIC ACID; GLYCERIN; METHYLPARABEN; PROPYLENE GLYCOL; PROPYLPARABEN; WATER; SODIUM ACETATE; SUCROSE

Drug Facts

Active ingredient (in each 5 mL teaspoonful)

Cetirizine Hydrochloride USP 5 mg

Purpose

Antihistamine

Uses

temporarily relieves these symptoms due to hay fever or other upper respiratory allergies:

- runny nose
- sneezing
- itchy, watery eyes
- itching of the nose or throat

Warnings

Do not use if you have ever had an allergic reaction to this product or any of its ingredients or to an antihistamine containing hydroxyzine.

Ask a doctor before use if you have

liver or kidney disease. Your doctor should determine if you need a different dose.

Ask a doctor or pharmacist before use if you are

taking tranquilizers or sedatives.

When using this product

- drowsiness may occur
- avoid alcoholic drinks
- alcohol, sedatives, and tranquilizers may increase drowsiness
- be careful when driving a motor vehicle or operating machinery.

Stop use and ask a doctor if

an allergic reaction to this product occurs. Seek medical help right away.

If pregnant or breast-feeding

- If breast-feeding: not recommended
- If pregnant: ask a health professional before use.

Keep out of reach of children.

In case of overdose, get medical help or contact a Poison Control Center right away (1-800-222-1222).

Directions

- use only with enclosed dosing cup
- mL=milliliter

adults and children 6 years and over | 1 teaspoonful (5 mL) or 2 teaspoonfuls (10 mL) once daily depending upon severity of symptoms; do not take more than 2 teaspoonfuls (10 mL) in 24 hours.
adults 65 years and over | 1 teaspoonful (5 mL) once daily; do not take more than 1 teaspoonful (5 mL) in 24 hours.
children 2 to under 6 years of age | 1/2 teaspoonful (2.5 mL) once daily. If needed, dose can be increased to a maximum of 1 teaspoonful (5 mL) once daily or 1/2 teaspoonful (2.5 mL) every 12 hours. Do not give more than 1 teaspoonful (5 mL) in 24 hours.
children under 2 years of age | ask a doctor
consumers with liver or kidney disease | ask a doctor

Other information

store between 20° to 25° C (68° to 77°F)

Inactive ingredients

banana flavor, glacial acetic acid, glycerin, grape flavor, methylparaben, propylene glycol, propylparaben, purified water, sodium acetate, sucrose

Questions?

call 1-855-274-4122
Distributed by:
Fred's, Inc.
4300 NEW GETWELL RD, MEMPHIS, TN 38118
www.fredsinc.com

fred’s Promise Not Happy With This Product? Just Bring It Back For a Refund!

PACKAGE LABEL- PRINCIPAL DISPLAY PANEL 4 FL OZ (120 mL Bottle)

NDC 55315-354-31
fred*s
KIDS®
2 yrs & older
Children's
Allergy
Relief
Indoor & Outdoor
Allergies

Cetirizine Hydrochloride
Oral Solution, USP 1mg/mL
Antihistamine
Grape Flavored Syrup
24 Hour Relief of:
Sneezing
Runny Nose
Itchy, Watery Eyes
Itchy Nose or Throat
Dosing Cup
Included
4 FL OZ (120 mL)
Compare to
*Children's ZYRTEC®